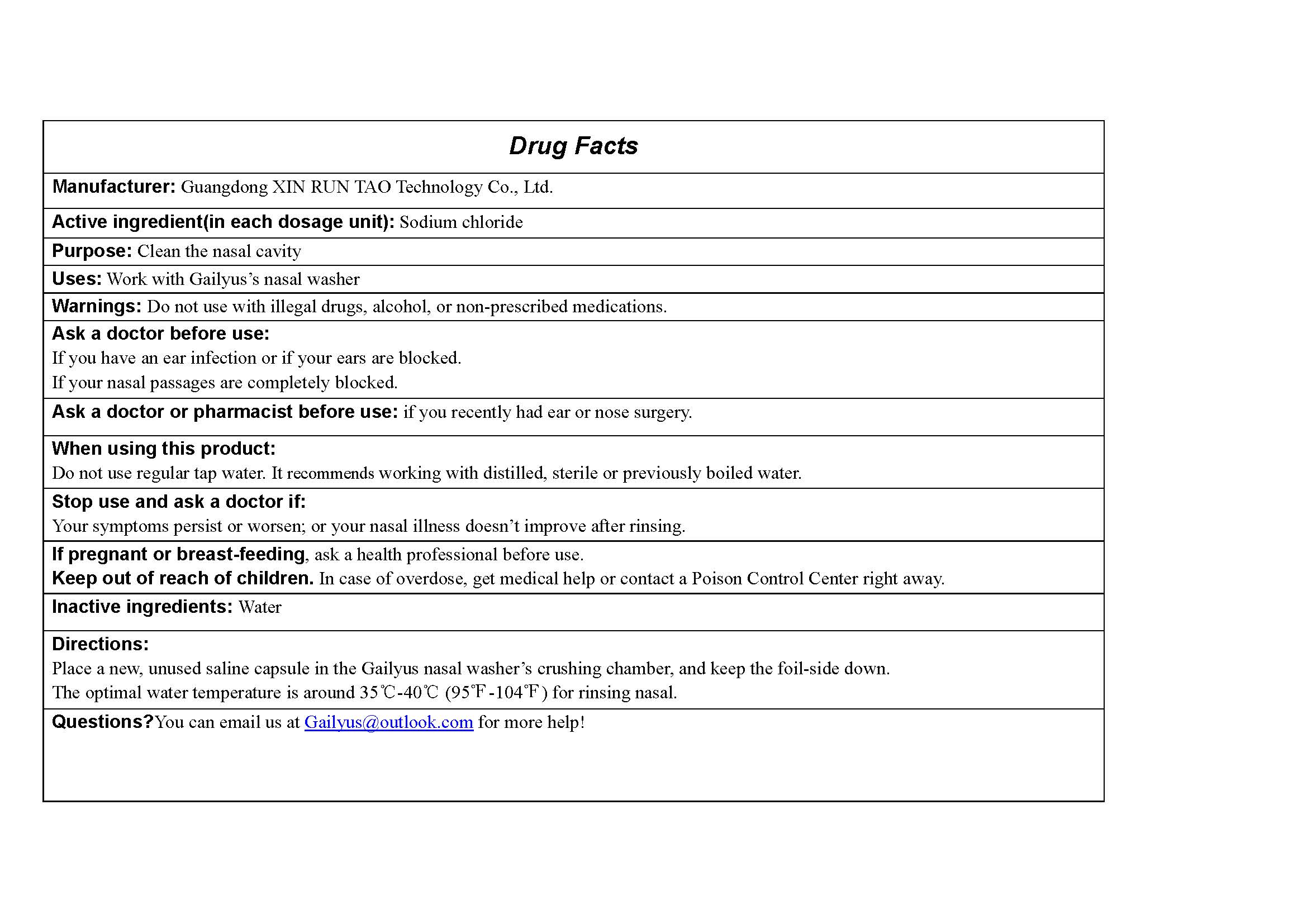 DRUG LABEL: nasal wash saline
NDC: 83660-001 | Form: LIQUID
Manufacturer: Shenzhen Jun&Liang Media Tech Limited
Category: otc | Type: HUMAN OTC DRUG LABEL
Date: 20230831

ACTIVE INGREDIENTS: SODIUM CHLORIDE 245 mg/9.5 mL
INACTIVE INGREDIENTS: WATER 7.1725 mL/9.5 mL

Active ingredient(in each dosage unit): Sodium chloride

Purpose: Clean the nasal cavity

INDICATIONS AND USAGE

Uses: Work with Gailyus’s nasal washer

WARNINGS

Warnings: Do not use with illegal drugs, alcohol, or non-prescribed medications

Ask a doctor before use:
If you have an ear infection or if your ears are blocked.
If your nasal passages are completely blocked.

Ask a doctor or pharmacist before use: if you recently had ear or nose surgery.

When using this product:
Do not use regular tap water. It recommends working with distilled, sterile or previously boiled water.

Stop use and ask a doctor if:
Your symptoms persist or worsen; or your nasal illness doesn’t improve after rinsing.

PREGNANCY OR BREAST FEEDING

If pregnant or breast-feeding, ask a health professional before use.

Keep out of reach of children. In case of overdose, get medical help or contact a Poison Control Center right away.

INACTIVE INGREDIENT

Water

Directions:
Place a new, unused saline capsule in the Gailyus nasal washer’s crushing chamber, and keep the foil-side down.
The optimal water temperature is around 35℃-40℃ (95℉-104℉) for rinsing nasal.

QUESTIONS

Questions?You can email us at Gailyus@outlook.com for more help!

DOSAGE AND ADMINISTRATION

Place a new, unused saline capsule in the Gailyus nasal washer’s crushing chamber, and keep the foil-side down.
The optimal water temperature is around 35℃-40℃ (95℉-104℉) for rinsing nasal.

label